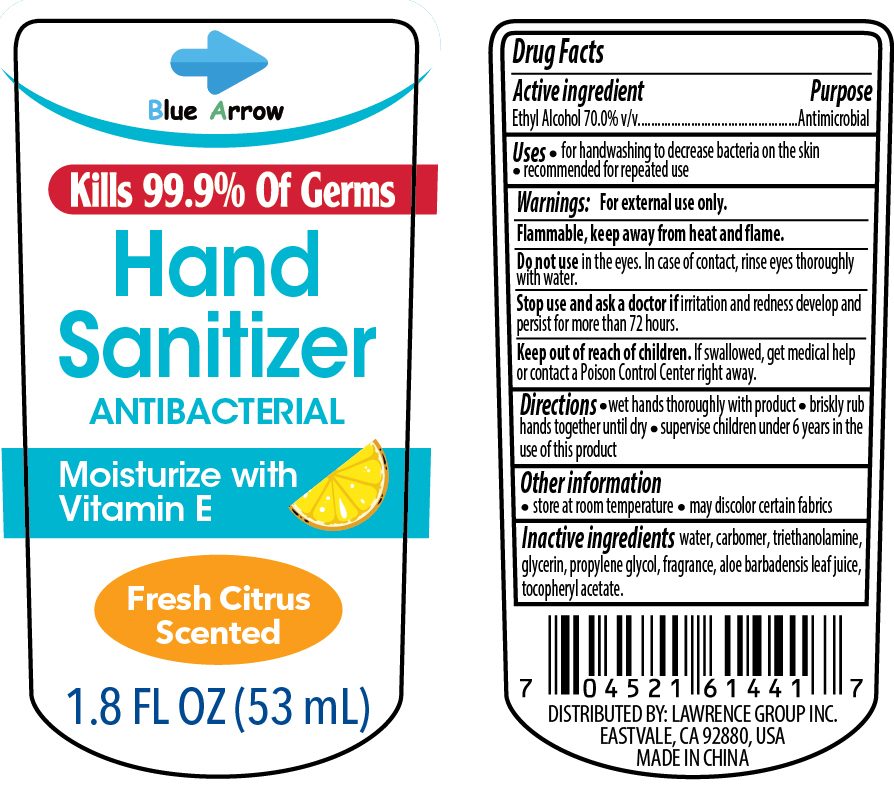 DRUG LABEL: Blue Arrow Hand Sanitizer 1.8oz
NDC: 58503-148 | Form: LIQUID
Manufacturer: China Ningbo Shangge Technology Co., Ltd.
Category: otc | Type: HUMAN OTC DRUG LABEL
Date: 20200909

ACTIVE INGREDIENTS: ALCOHOL 70 mL/100 mL
INACTIVE INGREDIENTS: CARBOMER HOMOPOLYMER, UNSPECIFIED TYPE; PROPYLENE GLYCOL; ALPHA-TOCOPHEROL ACETATE; GLYCERIN; WATER; TROLAMINE; ALOE VERA LEAF

Active Ingredient(s)

Ethyl Alcohol 70% v/v

Purpose

Antimicrobial

Use

- For handwashing to decrease bacteria on the skin
- recommended for repeated use

Warnings

For external use only. Flammable, keep away from heat and flame.

Do not use

- in the eyes. in case of contact, rinse eyes thoroughly with water.

Stop use and ask a doctor if irritation and redness develop and persist for more than 72 hours.

Keep out of reach of children. If swallowed, get medical help or contact a Poison Control Center right away.

Directions

- Wet hands thoroughly with product
- briskly rub hands together until dry
- Supervise children under 6 years in the use of this product

Other information

- Store at room temperature
- may discolor certain fabrics

Inactive ingredients

water, carbomer, triethanolamine, glycerin, propylene glycol, fragrance, aloe barbadensis leaf juice, tocopheryl acetate

Package Label - Principal Display Panel

000 mL NDC: 00000-000-00